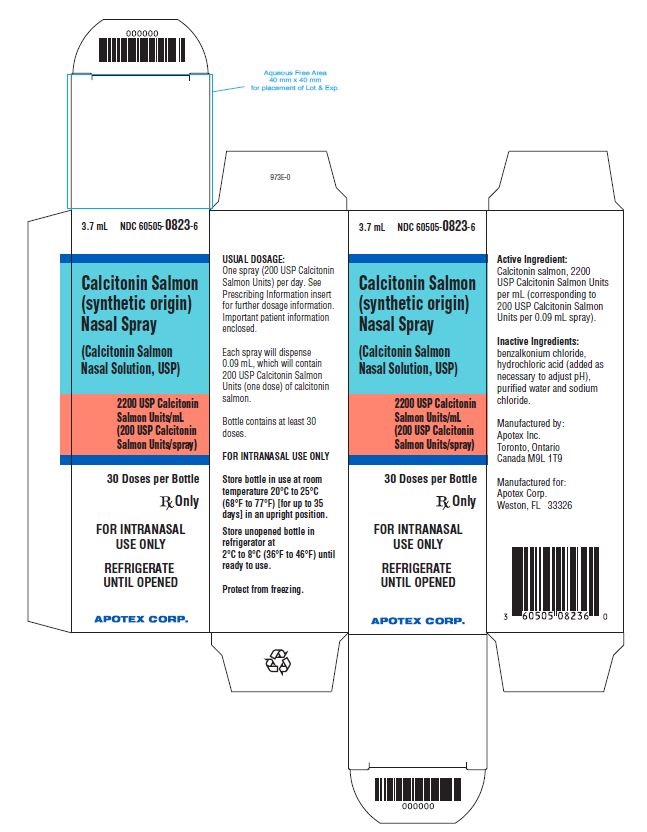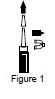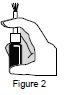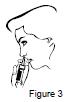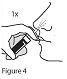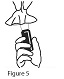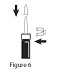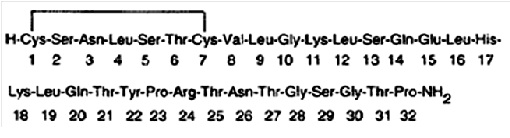 DRUG LABEL: Calcitonin Salmon
NDC: 60505-0823 | Form: SPRAY, METERED
Manufacturer: Apotex  Corp.
Category: prescription | Type: HUMAN PRESCRIPTION DRUG LABEL
Date: 20250917

ACTIVE INGREDIENTS: CALCITONIN SALMON 200 [iU]/1 1
INACTIVE INGREDIENTS: BENZALKONIUM CHLORIDE; HYDROCHLORIC ACID; WATER; SODIUM CHLORIDE

HIGHLIGHTS OF PRESCRIBING INFORMATION

These highlights do not include all the information needed to use CALCITONIN SALMON NASAL SPRAY safely and effectively. See full prescribing information for CALCITONIN SALMON NASAL SPRAY.
CALCITONIN SALMON nasal spray
Initial U.S. Approval: 1975

1 INDICATIONS AND USAGE

Calcitonin Salmon (synthetic origin) Nasal Spray is a calcitonin, indicated for the treatment of postmenopausal osteoporosis in women greater than 5 years postmenopause when alternative treatments are not suitable. Fracture reduction efficacy has not been demonstrated (1.1)

Limitations of Use:

- Due to the possible association between malignancy and calcitonin salmon use, the need for continued therapy should be re-evaluated on a periodic basis (1.2, 5.4)
- Calcitonin salmon nasal spray has not been shown to increase bone mineral density in early postmenopausal women (1.2)

2 DOSAGE AND ADMINISTRATION

- For intranasal use only: one spray (200 USP Calcitonin Salmon Units) per day, alternating nostrils daily (2.1)
- Prior to first use, allow the bottle to reach room temperature and prime the pump (2.2)
- Ensure adequate calcium and vitamin D intake (2.3)

3 DOSAGE FORMS AND STRENGTHS

Nasal Spray: 2200 USP Calcitonin Salmon Units per mL of calcitonin salmon in a 2 mL or 3.7 mL fill glass bottle with attached pump. Each actuation delivers 200 USP Calcitonin Salmon Units of calcitonin salmon (3)

4 CONTRAINDICATIONS

Hypersensitivity to calcitonin salmon or any of the excipients (4)

5 WARNINGS AND PRECAUTIONS

- Serious hypersensitivity reactions including anaphylactic shock have been reported. Consider skin testing prior to treatment in patients with suspected hypersensitivity to calcitonin salmon (5.1)
- Hypocalcemia has been reported. Ensure adequate intake of calcium and vitamin D (5.2)
- Nasal adverse reactions, including severe ulceration can occur. Periodic nasal examinations are recommended (5.3)
- Malignancy: A meta-analysis of 21 clinical trials suggests an increased risk of overall malignancies in calcitonin salmon-treated patients (5.4, 6.1)
- Circulating antibodies to calcitonin salmon may develop, and may cause loss of response to treatment (5.5)

6 ADVERSE REACTIONS

Most common adverse reactions (3% or greater) are rhinitis, epistaxis and other nasal symptoms, back pain, arthralgia, and headache (6)

To report SUSPECTED ADVERSE REACTIONS, contact Apotex Corp. at 1-800-706-5575 or FDA at 1-800-FDA-1088 or www.fda.gov/medwatch.

7 DRUG INTERACTIONS

- Concomitant use of calcitonin salmon and lithium may lead to a reduction in plasma lithium concentrations due to increased urinary clearance of lithium. The dose of lithium may require adjustment (7)

8 USE IN SPECIFIC POPULATIONS

- There are no data to support use in children (8.4)
- Nasal reactions are more common in elderly patients (8.5)

FULL PRESCRIBING INFORMATION

1 INDICATIONS AND USAGE

1.1 Treatment of Postmenopausal Osteoporosis

Calcitonin Salmon (synthetic origin) Nasal Spray is indicated for the treatment of postmenopausal osteoporosis in women greater than 5 years postmenopause. Fracture reduction efficacy has not been demonstrated. Calcitonin Salmon (synthetic origin) Nasal Spray should be reserved for patients for whom alternative treatments are not suitable (e.g., patients for whom other therapies are contraindicated or for patients who are intolerant or unwilling to use other therapies).

1.2 Important Limitations of Use

- Due to the possible association between malignancy and calcitonin salmon use, the need for continued therapy should be re-evaluated on a periodic basis [see Warnings and Precautions (5.4)].
- Calcitonin Salmon (synthetic origin) Nasal Spray has not been shown to increase spinal bone mineral density in early postmenopausal women.

2 DOSAGE AND ADMINISTRATION

2.1 Basic Dosing Information

The recommended dose of calcitonin salmon nasal spray is 1 spray (200 USP Calcitonin Salmon Units) per day administered intranasally, alternating nostrils daily.

2.2 Priming (Activation) of Pump

Unopened calcitonin salmon nasal spray should be stored in the refrigerator. Before using the first dose of calcitonin salmon nasal spray, the patient should wait until it has reached room temperature. To prime the pump before it is used for the first time, the bottle should be held upright and the two white side arms of the pump depressed toward the bottle, repeat until a full spray is released. The pump is primed once the first full spray is emitted. To administer, the nozzle should first be carefully placed into the nostril while the patient’s head is in the upright position, then the pump should be firmly depressed toward the bottle. The pump should not be primed before each daily dose.

2.3 Recommendations for Calcium and Vitamin D Supplementation

Patients who use calcitonin salmon nasal spray should receive adequate calcium (at least 1000 mg elemental calcium per day) and vitamin D (at least 400 International Units per day).

3 DOSAGE FORMS AND STRENGTHS

Calcitonin Salmon (synthetic origin) Nasal Spray consists of one glass bottle with attached pump. The bottle contains 2 mL or 3.7 mL of calcitonin salmon clear solution at a concentration of 2200 USP Calcitonin Salmon Units per mL. A primed pump delivers 0.09 mL (200 USP Calcitonin Salmon Units) calcitonin salmon per actuation.

4 CONTRAINDICATIONS

Hypersensitivity to calcitonin salmon or any of the excipients. Reactions have included anaphylactic shock, anaphylaxis, bronchospasm, and swelling of the tongue or throat [see Warnings and Precautions (5.1)].

5 WARNINGS AND PRECAUTIONS

5.1 Hypersensitivity Reactions

Serious hypersensitivity reactions have been reported in patients receiving calcitonin salmon nasal spray, e.g., bronchospasm, swelling of the tongue or throat, anaphylaxis and anaphylactic shock. Reports of serious hypersensitivity reactions with injectable calcitonin salmon have also been reported, including reports of death attributed to anaphylaxis. The usual provisions should be made for emergency treatment if such a reaction occurs. Hypersensitivity reactions should be differentiated from generalized flushing and hypotension [see Contraindications (4)].

For patients with suspected hypersensitivity to calcitonin salmon, skin testing should be considered prior to treatment utilizing a dilute, sterile solution of a calcitonin salmon injectable product. Healthcare providers may wish to refer patients who require skin testing to an allergist. A detailed skin testing protocol is available from the Customer Service department of Apotex Corp. (1-800-706-5575).

5.2 Hypocalcemia

Hypocalcemia associated with tetany (i.e., muscle cramps, twitching) and seizure activity has been reported with calcitonin therapy. Hypocalcemia must be corrected before initiating therapy with calcitonin salmon nasal spray. Other disorders affecting mineral metabolism (such as vitamin D deficiency) should also be effectively treated. In patients with these conditions, serum calcium and symptoms of hypocalcemia should be monitored during therapy with calcitonin salmon nasal spray. Use of calcitonin salmon nasal spray is recommended in conjunction with an adequate intake of calcium and vitamin D [see Dosage and Administration (2.3)].

5.3 Nasal Adverse Reactions

Adverse reactions related to the nose including rhinitis and epistaxis have been reported. Development of mucosal alterations may occur. Therefore, periodic nasal examinations with visualization of the nasal mucosa, turbinates, septum and mucosal blood vessels are recommended prior to start of treatment with calcitonin salmon nasal spray, periodically during the course of therapy, and at any time nasal symptoms occur.

Calcitonin salmon nasal spray should be discontinued if severe ulceration of the nasal mucosa occurs, as indicated by ulcers greater than 1.5 mm in diameter or penetrating below the mucosa, or those associated with heavy bleeding. Although smaller ulcers often heal without withdrawal of calcitonin salmon nasal spray, medication should be discontinued temporarily until healing occurs [see Adverse Reactions (6.1)].

5.4 Malignancy

In a meta-analysis of 21 randomized, controlled clinical trials with calcitonin salmon (nasal spray or investigational oral formulations), the overall incidence of malignancies reported was higher among calcitonin salmon-treated patients (4.1%) compared with placebo-treated patients (2.9%). This suggests an increased risk of malignancies in calcitonin salmon-treated patients compared to placebo-treated patients. The benefits for the individual patient should be carefully considered against possible risks [see Adverse Reactions (6.1)].

5.5 Antibody Formation

Circulating antibodies to calcitonin salmon have been reported with calcitonin salmon nasal spray. The possibility of antibody formation should be considered in any patient with an initial response to calcitonin salmon nasal spray who later stops responding to treatment [see Adverse Reactions (6.3)].

5.6 Urine Sediment Abnormalities

Coarse granular casts and casts containing renal tubular epithelial cells were reported in young adult volunteers at bed rest who were given injectable calcitonin salmon to study the effect of immobilization on osteoporosis. There was no other evidence of renal abnormality and the urine sediment normalized after calcitonin salmon was stopped. Periodic examinations of urine sediment should be considered. Urine sediment abnormalities have not been reported in ambulatory volunteers treated with calcitonin salmon nasal spray.

6 ADVERSE REACTIONS

The following serious adverse reactions are discussed in greater detail in other sections of the label:

- Hypersensitivity Reactions, including anaphylaxis [see Warnings and Precautions (5.1)]
- Hypocalcemia [see Warnings and Precautions (5.2)]
- Nasal Adverse Reactions [see Warnings and Precautions (5.3)]
- Malignancy [see Warnings and Precautions (5.4)]

6.1 Clinical Trials Experience

Because clinical trials are conducted under widely varying conditions, adverse reaction rates observed in the clinical trials of a drug cannot be directly compared to rates in the clinical trials of another drug and may not reflect the rates observed in practice.

The safety of calcitonin salmon nasal spray in the treatment of postmenopausal osteoporosis was assessed in 5 randomized, double-blind, placebo controlled trials that enrolled postmenopausal women, aged 45 to 75 years. The duration of the trials ranged from 1 to 2 years. The incidence of adverse reactions reported in studies involving postmenopausal osteoporotic patients chronically exposed to calcitonin salmon nasal spray (N=341) and to placebo nasal spray (N=131), and reported in greater than 3% of calcitonin salmon nasal spray treated patients are presented in the following table. Other than flushing, nausea, possible allergic reactions, and possible local irritative effects in the respiratory tract, a relationship to calcitonin salmon nasal spray has not been established.

Table 1: Adverse Reactions Occurring in at Least 3% of Postmenopausal Patients Treated with Calcitonin Salmon Nasal Spray
 | Calcitonin Salmon Nasal Spray | Placebo Nasal Spray
Adverse Reaction | N=341 % of Patients | N=131 % of Patients
Rhinitis | 12 | 7
Symptom of Nose† | 11 | 16
Back Pain | 5 | 2
Arthralgia | 4 | 5
Epistaxis | 4 | 5
Headache | 3 | 5
†Symptom of nose includes: nasal crusts, dryness, redness or erythema, nasal sores, irritation, itching, thick feeling, soreness, pallor, infection, stenosis, runny/blocked, small wound, bleeding wound, tenderness, uncomfortable feeling and sore across bridge of nose.

Nasal Adverse Reactions
In all postmenopausal patients treated with calcitonin salmon nasal spray, the most commonly reported nasal adverse reactions included rhinitis (12%), epistaxis (4%), and sinusitis (2%). Smoking did not have a contributory effect on the occurrence of nasal adverse reactions.

Adverse reactions reported in 1% to 3% of patients treated with calcitonin salmon nasal spray include: influenza-like symptoms, erythematous rash, arthrosis, myalgia, sinusitis, upper respiratory tract infection, bronchospasm, abdominal pain, nausea, dizziness, paresthesia, abnormal lacrimation, conjunctivitis, lymphadenopathy, infection, and depression.

Malignancy
A meta-analysis of 21 randomized, controlled clinical trials with calcitonin salmon (nasal spray or investigational oral formulations) was conducted to assess the risk of malignancies in calcitonin salmon-treated patients compared to placebo-treated patients. The trials in the meta-analysis ranged in duration from 6 months to 5 years and included a total of 10883 patients (6151 treated with calcitonin salmon and 4732 treated with placebo). The overall incidence of malignancies reported in these 21 trials was higher among calcitonin salmon-treated patients (254/6151 or 4.1%) compared with placebo-treated patients (137/4732 or 2.9%). Findings were similar when analyses were restricted to the 18 nasal spray only trials [calcitonin salmon 122/2712 (4.5%); placebo 30/1309 (2.3%)].

The meta-analysis results suggest an increased risk of overall malignancies in calcitonin salmon-treated patients compared to placebo-treated patients when all 21 trials are included and when the analysis is restricted to the 18 nasal spray only trials (see Table 2). It is not possible to exclude an increased risk when calcitonin salmon is administered by the subcutaneous, intramuscular, or intravenous route because these routes of administration were not investigated in the meta-analysis. The increased malignancy risk seen with the meta-analysis was heavily influenced by a single large 5-year trial, which had an observed risk difference of 3.4% [95% CI (0.4%, 6.5%)]. Imbalances in risks were still observed when analyses excluded basal cell carcinoma (see Table 2); the data were not sufficient for further analyses by type of malignancy. A mechanism for these observations has not been identified. Although a definitive causal relationship between calcitonin salmon use and malignancies cannot be established from this meta-analysis, the benefits for the individual patient should be carefully evaluated against all possible risks [see Warnings and Precautions (5.4)].

Table 2: Risk Difference for Malignancies in Calcitonin Salmon-Treated Patients Compared with Placebo-Treated Patients
Patients | Malignancies | Risk Difference^1 (%) | 95% Confidence Interval^2 (%)
All (nasal spray + oral) | All | 1.0 | (0.3, 1.6)
All (nasal spray + oral) | Excluding basal cell carcinoma | 0.5 | (-0.1, 1.2)
All (nasal spray only) | All | 1.4 | (0.3, 2.6)
All (nasal spray only) | Excluding basal cell carcinoma | 0.8 | (-0.2, 1.8)
^1 The overall adjusted risk difference is the difference between the percentage of patients who had any malignancy (or malignancy excluding basal cell carcinoma) in calcitonin salmon and placebo treatment groups, using the Mantel-Haenszel (MH) fixed-effect method. A risk difference of 0 is suggestive of no difference in malignancy risks between the treatment groups.
^2 The corresponding 95% confidence interval for the overall adjusted risk difference also based on MH fixed-effect method.

6.2 Postmarketing Experience

Because postmarketing adverse reactions are reported voluntarily from a population of uncertain size, it is not always possible to reliably estimate their frequency or establish a causal relationship to drug exposure.

The following adverse reactions have been reported during post-approval use of calcitonin salmon nasal spray.

Allergic / Hypersensitivity Reactions
Serious allergic reactions have been reported in patients receiving calcitonin salmon nasal spray, including anaphylaxis and anaphylactic shock.

Hypocalcemia
Hypocalcemia with paresthesia has been reported.

Body as a whole
facial or peripheral edema

Cardiovascular
hypertension, vasodilatation, syncope, chest pain

Nervous system
dizziness, seizure, visual or hearing impairment, tinnitus

Respiratory/Special Senses
cough, bronchospasm, dyspnea, loss of taste/smell

Skin
rash/dermatitis, pruritus, alopecia, increased sweating

Gastrointestinal
diarrhea

Nervous system disorders
tremor

6.3 Immunogenicity

Consistent with the potentially immunogenic properties of medicinal products containing peptides, administration of calcitonin salmon nasal spray may trigger the development of anti-calcitonin antibodies. In a two-year calcitonin salmon nasal spray clinical study that evaluated immunogenicity, a measurable antibody titer was found in 69% of patients treated with calcitonin salmon nasal spray and 3% of placebo-treated patients. Antibody formation may be associated with a loss of response to treatment [see Warnings and Precautions (5.5)].

The incidence of antibody formation is highly dependent on the sensitivity and specificity of the assay. Additionally, the observed incidence of a positive antibody test result may be influenced by several factors, including assay methodology, sample handling, timing of sample collection, concomitant medications, and underlying disease. For these reasons, comparison of antibodies to calcitonin salmon nasal spray with the incidence of antibodies to other calcitonin-containing products may be misleading.

7 DRUG INTERACTIONS

No formal drug interaction studies have been performed with calcitonin salmon nasal spray.

Concomitant use of calcitonin salmon and lithium may lead to a reduction in plasma lithium concentrations due to increased urinary clearance of lithium. The dose of lithium may require adjustment.

8 USE IN SPECIFIC POPULATIONS

8.1 Pregnancy

Risk Summary

Calcitonin salmon nasal spray is not indicated for use in females of reproductive potential. There are no data with the use of calcitonin salmon nasal spray in pregnant women. In an animal reproduction study, subcutaneous administration of calcitonin-salmon to pregnant rabbits during organogenesis at 418 times the recommended parenteral human dose caused a decrease in fetal birth weights. No adverse developmental outcome was observed in the rat with subcutaneous administration of calcitonin-salmon at 9 times the recommended human parenteral dose based on body surface area (see Data).

Data

Animal Data

Calcitonin salmon has been shown to cause a decrease in fetal birth weights in rabbits when given by subcutaneous injection in doses 4 to 18 times the parenteral dose (of 54 International Units/m^2) and 70 to 278 times the intranasal dose recommended for human use based on body surface area.

No embryo/fetal toxicities related to calcitonin salmon nasal spray were reported from maternal subcutaneous daily doses in rats up to 80 International Units/kg/day from gestation day 6 to 15.

8.2 Lactation

Risk Summary

Calcitonin salmon nasal spray is not indicated for use in females of reproductive potential. There is no information on the presence of calcitonin-salmon in human milk, the effects on the breastfed child, or the effects on milk production. Calcitonin has been shown to inhibit lactation in rats.

8.4 Pediatric Use

Safety and effectiveness in pediatric patients have not been established.

8.5 Geriatric Use

In a multi-centered, double-blind, randomized clinical study of calcitonin salmon nasal spray, 279 patients were less than 65 years old, while 467 patients were 65 to 74 years old and 196 patients were 75 years old and older. Compared to subjects less than 65 years old, the incidence of nasal adverse reactions (rhinitis, irritation, erythema, and excoriation) was higher in patients over the age of 65, particularly among those over the age of 75. Other reported clinical experience has not identified differences in responses between the elderly and younger patients, but greater sensitivity of some older individuals cannot be ruled out.

10 OVERDOSAGE

The pharmacologic actions of calcitonin salmon nasal spray suggest that hypocalcemic tetany could occur in overdose. Therefore, provisions for parenteral administration of calcium should be available for the treatment of overdose.

Single doses of calcitonin salmon nasal spray up to 1600 International Units, doses up to 800 International Units per day for 3 days and chronic administration of doses up to 600 International Units per day have been studied without serious adverse effects.

11 DESCRIPTION

Calcitonin is a polypeptide hormone secreted by the parafollicular cells of the thyroid gland in mammals and by the ultimobranchial gland of birds and fish.

Calcitonin Salmon (synthetic origin) Nasal Spray is a synthetic polypeptide of 32 amino acids in the same linear sequence that is found in calcitonin of salmon origin. This is shown by the following graphic formula:

It is provided in a 2 mL or 3.7 mL fill glass bottle as a solution for nasal administration. This is sufficient medication for at least 14 doses (2 mL fill) or 30 doses (3.7 mL fill).

Active Ingredient: calcitonin salmon 2200 USP Calcitonin Salmon Units per mL (corresponding to 200 USP Calcitonin Salmon Units per 0.09 mL actuation).

Inactive Ingredients: benzalkonium chloride, hydrochloric acid (added as necessary to adjust pH), purified water and sodium chloride.

The activity of calcitonin salmon nasal spray is stated in International Units based on bioassay in comparison with the International Reference Preparation of calcitonin salmon for Bioassay, distributed by the National Institute of Biological Standards and Control, Holly Hill, London.

12 CLINICAL PHARMACOLOGY

12.1 Mechanism of Action

Calcitonin salmon is a calcitonin receptor agonist. Calcitonin salmon acts primarily on bone, but direct renal effects and actions on the gastrointestinal tract are also recognized. Calcitonin salmon appears to have actions essentially identical to calcitonins of mammalian origin, but its potency per mg is greater and it has a longer duration of action.

The actions of calcitonin on bone and its role in normal human bone physiology are still not completely elucidated, although calcitonin receptors have been discovered in osteoclasts and osteoblasts.

12.2 Pharmacodynamics

The information below, describing the clinical pharmacology of calcitonin, has been derived from studies with injectable calcitonin salmon. The mean bioavailability of calcitonin salmon nasal spray is approximately 3% of the injectable calcitonin salmon in healthy subjects and, therefore, the conclusions concerning the clinical pharmacology of this preparation may be different.

Bone
Single injections of calcitonin salmon caused a marked transient inhibition of the ongoing bone resorptive process. With prolonged use, there is a persistent, smaller decrease in the rate of bone resorption. Histologically, this is associated with a decreased number of osteoclasts and an apparent decrease in their resorptive activity.

In healthy adults, who have a relatively low rate of bone resorption, the administration of exogenous calcitonin salmon results in decreases in serum calcium within the limits of the normal range. In healthy children and in patients whose bone resorption is more rapid, decreases in serum calcium are more pronounced in response to calcitonin salmon.

Kidney
Studies with injectable calcitonin salmon show increases in the excretion of filtered phosphate, calcium, and sodium by decreasing their tubular reabsorption. Comparable studies have not been conducted with calcitonin salmon nasal spray.

Gastrointestinal Tract
Some evidence from studies with injectable preparations suggests that calcitonin salmon may have effects on the gastrointestinal tract. Short-term administration of injectable calcitonin salmon results in marked transient decreases in the volume and acidity of gastric juice and in the volume and the trypsin and amylase content of pancreatic juice. Whether these effects continue to be elicited after each injection of calcitonin salmon during chronic therapy has not been investigated. These studies have not been conducted with calcitonin salmon nasal spray.

Calcium Homeostasis
In two clinical studies designed to evaluate the pharmacodynamic response to calcitonin salmon nasal spray, administration of calcitonin salmon 100 to 1600 International Units to healthy volunteers resulted in rapid and sustained decreases within the normal range for both total serum calcium and serum ionized calcium. Single doses of calcitonin salmon greater than 400 International Units did not produce any further biological response to the drug.

12.3 Pharmacokinetics

The bioavailability of calcitonin salmon nasal spray relative to intramuscular administration in healthy volunteers is between 3% and 5%. Calcitonin salmon nasal spray is absorbed rapidly by the nasal mucosa with a mean Tmax of about 13 minutes. The terminal half-life of calcitonin salmon has been calculated to be around 18 minutes and no evidence of accumulation was observed with multiple dosing.

13 NONCLINICAL TOXICOLOGY

13.1 Carcinogenesis, Mutagenesis, Impairment of Fertility

Carcinogenicity
The incidence of pituitary adenomas was increased in rats after one and two years of subcutaneous exposure to synthetic calcitonin salmon. The significance of this finding to humans is unknown because pituitary adenomas are very common in rats as they age, the pituitary adenomas did not transform into metastatic tumors, there were no other clear treatment-related neoplasms, and synthetic calcitonin salmon related neoplasms were not observed in mice after two years of dosing.

Rat findings
The only clear neoplastic finding in rats dosed subcutaneously with synthetic calcitonin salmon was an increase in the incidence of pituitary adenomas in male Fisher 344 rats and female Sprague Dawley rats after one year of dosing and male Sprague Dawley rats dosed for one and two years. In female Sprague Dawley rats, the incidence of pituitary adenomas after two years was high in all treatment groups (between 80% and 92% including the control groups) such that a treatment-related effect could not be distinguished from natural background incidence. The lowest dose in male Sprague Dawley rats that developed an increased incidence of pituitary adenomas after two years of dosing (1.7 International Units/kg/day) is approximately 2 times the maximum recommended intranasal dose in humans (200 International Units/day) based on body surface area conversion between rats and humans and a 20-fold conversion factor to account for decreased clinical exposure via the intranasal route. The findings suggest that calcitonin salmon reduced the latency period for development of non-functioning pituitary adenomas.

Mouse findings
No carcinogenicity potential was evident in male or female mice dosed subcutaneously for two years with synthetic calcitonin salmon at doses up to 800 International Units/kg/day. The 800 International Units/kg/day dose is approximately 390 times the maximum recommended intranasal dose in humans (200 International Units) based on scaling for body surface area and a 20-fold conversion factor to account for low clinical exposure via the intranasal route.

Mutagenesis
Synthetic calcitonin salmon tested negative for mutagenicity using Salmonella typhimurium (5 strains) and Escherichia coli (2 strains), with and without rat liver metabolic activation, and was not clastogenic in a chromosome aberration test in Chinese Hamster V79 cells. There was no evidence that calcitonin salmon was clastogenic in the in vivo mouse micronucleus test.

Fertility
Effects of calcitonin salmon on fertility have not been assessed in animals.

14 CLINICAL STUDIES

Two randomized, placebo-controlled, two-year trials were conducted in 266 postmenopausal women who were greater than 5 years postmenopause with spinal, forearm or femoral bone mineral density (BMD) at least one standard deviation below the normal value for healthy premenopausal women (T-score < -1). In both studies, a total of 144 patients received calcitonin salmon nasal spray 200 International Units or placebo daily. The intent-to-treat population comprised 139 patients who had at least one follow-up BMD measurement. In study 1, patients also received 500 mg daily calcium supplements, while in study 2, patients received no calcium supplementation. The primary endpoint for both studies was percent change in lumbar spine BMD at 2 years. Calcitonin salmon nasal spray increased lumbar vertebral BMD relative to placebo in women with low bone mass who were greater than 5 years post menopause (see Table 3 below).

Table 3: Calcitonin Salmon Nasal Spray: Lumbar Spine Bone Mineral Density In Women Greater Than 5 years Postmenopause With Low Bone Mass
 | Lumbar Spine Bone Mineral Density, Mean Change From Baseline (in %) at Month 24
 | Study 1 (with calcium supplement) n (ITT) = 100 | Study 2 (no calcium supplement) n (ITT) = 39
Calcitonin Salmon 200 IU NS daily | +1.56 | +1.02
Placebo | +0.20 | -1.85
Treatment Difference | +1.36 | +2.87
p-value† | < 0.05 | < 0.005
ITT: Intent To Treat
IU: International Units
NS: nasal spray
†p-values by parametric testing (2-tailed 2-sample t-test)

No effects of calcitonin salmon nasal spray on cortical bone of the forearm or hip were demonstrated.

In clinical studies of postmenopausal osteoporosis, bone biopsy and radial bone mass assessments at baseline and after 26 months of daily injectable calcitonin salmon indicate that calcitonin therapy results in the formation of normal bone.

16 HOW SUPPLIED/STORAGE AND HANDLING

How Supplied
Calcitonin Salmon (synthetic origin) Nasal Spray is available as a metered dose clear solution in a 2 mL or 3.7 mL fill clear glass bottle that contains 2,200 USP Calcitonin Salmon Units calcitonin salmon per mL. A pump is attached to the bottle. After priming, the pump will deliver 200 USP Calcitonin Salmon Units per activation (0.09 mL per spray) (2 mL fill: NDC 60505-0823-0; 3.7 mL fill: NDC 60505-0823-6).

Storage and Handling
Store unopened bottle in refrigerator between 2°C to 8°C (36°F to 46°F). Protect from freezing.

Store bottle in use at room temperature between 20°C to 25°C (68°F to 77°F) in an upright position, for up to 30 days (2 mL fill) or 35 days (3.7 mL fill). Each bottle contains at least 14 doses (2 mL fill) or 30 doses (3.7 mL fill).

Discard bottle after 14 doses (2 mL fill) or 30 doses (3.7 mL fill).

17 PATIENT COUNSELING INFORMATION

See FDA-approved patient labeling (Patient Information and Instructions for Use).

- Instruct patients on pump assembly, priming of the pump, and nasal introduction of Calcitonin Salmon (synthetic origin) Nasal Spray. Although instructions for patients are supplied with the individual bottle, procedures for use should be demonstrated to each patient [see Dosage and Administration (2.2)]. Patients should notify their healthcare provider if they develop significant nasal irritation [see Warnings and Precautions (5.3)].
- Inform patients of the potential increase in risk of malignancy [see Warnings and Precautions (5.4)].
- Advise patients to maintain an adequate calcium (at least 1000 mg elemental calcium per day) and vitamin D (at least 400 International Units per day) intake [see Dosage and Administration (2.3)].
- Instruct patients to seek emergency medical help or go to the nearest hospital emergency room right away if they develop any signs or symptoms of a serious allergic reaction.
- Advise patients how to correctly store unopened and opened product [see How Supplied/Storage and Handling (16)]. Advise patients that the bottle should be discarded after 14 doses (2 mL fill) or 30 doses (3.7 mL fill), because after 14 or 30 doses, each spray may not deliver the correct amount of medication even if the bottle is not completely empty.

APOTEX INC.
CALCITONIN SALMON (SYNTHETIC ORIGIN) NASAL SPRAY

Manufactured by | Manufactured for
Apotex Inc. | Apotex Corp.
Toronto, Ontario | Weston, FL
Canada M9L 1T9 | 33326

Revised: November 2017

INSTRUCTIONS FOR USE

Calcitonin Salmon (synthetic origin)

(kal" si toe' nin)

Nasal Spray

For Nasal Use Only.

Important information about your Calcitonin Salmon (synthetic origin) Nasal Spray:

- A single spray of Calcitonin Salmon (synthetic origin) Nasal Spray contains 1 daily dose of medicine.
- Each Calcitonin Salmon (synthetic origin) Nasal Spray bottle contains the right amount of medicine. The bottle may not be completely filled to the top. This is normal.
- This package contains 1 bottle of Calcitonin Salmon (synthetic origin) Nasal Spray with attached pump.
- Store unopened bottles of Calcitonin Salmon (synthetic origin) Nasal Spray in the refrigerator between 2°C to 8°C (36°F to 46°F). Do not freeze.
- After you open your bottle of Calcitonin Salmon (synthetic origin) Nasal Spray, store it at room temperature between 20°C to 25°C (68°F to 77°F) in an upright position. Do not shake the bottle.

Preparing your Calcitonin Salmon (synthetic origin) Nasal Spray:

Step 1. Remove the bottle from your refrigerator and let it reach room temperature. Check the medicine in the bottle to make sure it is clear and colorless without particles.

Step 2. Remove the clear plastic dust cap and the blue safety clip from the nasal spray pump. See Figure 1. The safety clip prevents the accidental discharge of the spray in your pocket or purse.

Step 3. Check to see if your Calcitonin Salmon (synthetic origin) Nasal Spray has been primed.

- To make sure you get the right dose of Calcitonin Salmon (synthetic origin) Nasal Spray medicine you must prime each new bottle and pump before you use it for the first time.
- Check to see if the bottle and pump has already been primed by pressing on the pump 1 time. See Figure 2.
- If you see a full spray from the pump, the bottle and pump has already been primed for you.
- If you do not see a full spray, you must prime the bottle and pump.

Step 4. Priming your Calcitonin Salmon (synthetic origin) Nasal Spray:

- Hold the bottle upright with your pointer finger and middle finger on the 2 side arms of the pump, and your thumb on the bottom of the bottle. Firmly press down on the arms of the pump and press down again if needed until you see a full spray of medicine. See Figure 2.
- Now your Calcitonin Salmon (synthetic origin) Nasal Spray is ready for you to use.
- Do not prime the pump before you use it each day because this will waste your medicine.

Giving your Calcitonin Salmon (synthetic origin) Nasal Spray dose:

Step 5. Insert the nasal spray pump in 1 side of your nose. See Figure 3.

- Keep your head upright. Carefully tilt the bottle and place the nose spray pump into 1 side of your nose.

Step 6. Firmly press down on the nose spray pump to release the medicine. See Figure 4.

- Give 1 spray of Calcitonin Salmon (synthetic origin) Nasal Spray, 1 time daily, in 1 side of your nose (nostril). Spray your medicine in a different side of your nose each day.
- You do not need to breathe or inhale while you are giving your dose.
- You may not feel the spray inside your nose.
- Some of the medicine may drip out of your nose. This is normal, and you are still getting all of the medicine you need.

Cleaning your Calcitonin Salmon (synthetic origin) Nasal Spray pump:

Step 7. Wipe the nose spray pump with a clean, damp cloth 1 to 2 times a week. See Figure 5.

- Dry the nose spray pump with a clean cloth.

Storing your Calcitonin Salmon (synthetic origin) Nasal Spray:

Step 8. Replace the blue safety clip, then replace the protective cap on the nasal spray unit. See Figure 6.

- Be careful not to push down on the pump while you are putting the cap back on it.
- Do not refrigerate Calcitonin Salmon (synthetic origin) Nasal Spray between doses.
- Store Calcitonin Salmon (synthetic origin) Nasal Spray upright.
- Do not shake the bottle.

When should I throw away Calcitonin Salmon (synthetic origin) Nasal Spray?

- Unopened, refrigerated bottles can be used until the expiration date stamped on the bottle and box.
- Throw away Calcitonin Salmon (synthetic origin) Nasal Spray after you use 14 doses (2 mL fill) or 30 doses (3.7 mL fill) (sprays).
- Throw away Calcitonin Salmon (synthetic origin) Nasal Spray bottles left at room temperature (opened or unopened) for more than 30 days (2 mL fill) or 35 days (3.7 mL fill).

For more information on Calcitonin Salmon (synthetic origin) Nasal Spray, call Apotex Corp. at 1-800-706-5575.

This Patient Information and Instructions for Use has been approved by the U.S. Food and Drug Administration.

APOTEX INC.
CALCITONIN SALMON (SYNTHETIC ORIGIN) NASAL SPRAY

Manufactured by | Manufactured for
Apotex Inc. | Apotex Corp.
Toronto, Ontario | Weston, FL
Canada M9L 1T9 | 33326

Revised: November 2017

PATIENT INFORMATION

Calcitonin Salmon (synthetic origin)

(kal" si toe' nin)

Nasal Spray

Read this Patient Information before you start using Calcitonin Salmon (synthetic origin) Nasal Spray and each time you get a refill. There may be new information. This information does not take the place of talking to your healthcare provider about your medical condition or your treatment.

What is Calcitonin Salmon (synthetic origin) Nasal Spray?

Calcitonin Salmon (synthetic origin) Nasal Spray is a prescription medicine used to treat osteoporosis in women more than 5 years after menopause. Calcitonin Salmon (synthetic origin) Nasal Spray should be used for women who cannot use other treatments or who choose not to use other treatments for osteoporosis.

It is not known if Calcitonin Salmon (synthetic origin) Nasal Spray lowers the chance of having bone fractures.

Calcitonin Salmon (synthetic origin) Nasal Spray has not been shown to be effective in women less than 5 years after menopause.

It is not known if Calcitonin Salmon (synthetic origin) Nasal Spray is safe and effective in children under 18 years of age.

Who should not use Calcitonin Salmon (synthetic origin) Nasal Spray?

Do not use Calcitonin Salmon (synthetic origin) Nasal Spray if you:

- are allergic to calcitonin salmon or any of the ingredients in Calcitonin Salmon (synthetic origin) Nasal Spray. See the end of this leaflet for a complete list of ingredients in Calcitonin Salmon (synthetic origin) Nasal Spray.

What should I tell my healthcare provider before using Calcitonin Salmon (synthetic origin) Nasal Spray?

Before you use Calcitonin Salmon (synthetic origin) Nasal Spray, tell your healthcare provider if you:

- have any other medical conditions
- have low calcium levels in your blood
- are pregnant or plan to become pregnant. It is not known if Calcitonin Salmon (synthetic origin) Nasal Spray can harm your unborn baby.
- are breastfeeding or plan to breastfeed. It is not known if Calcitonin Salmon passes into your breast milk. You and your healthcare provider should decide if you will use Calcitonin Salmon (synthetic origin) Nasal Spray or breastfeed.

Tell your healthcare provider about all the medicines you take, including prescription and over-the-counter medicines, vitamins, and herbal supplements.

Especially tell your healthcare provider if you take:

- lithium. Your healthcare provider may need to change your dose of lithium while you use Calcitonin Salmon (synthetic origin) Nasal Spray.

Know the medicines you take. Keep a list of them to show your healthcare provider and pharmacist when you get a new medicine.

How should I use Calcitonin Salmon (synthetic origin) Nasal Spray?

- For detailed instructions, see the Instructions for Use at the end of this Patient Information leaflet.
- Use Calcitonin Salmon (synthetic origin) Nasal Spray exactly as your healthcare provider tells you to use it.
- Do not use Calcitonin Salmon (synthetic origin) Nasal Spray until your healthcare provider shows you and you understand how to use it correctly.
- Use 1 spray of Calcitonin Salmon (synthetic origin) Nasal Spray, 1 time each day, in 1 nostril (inside your nose).
  - Start with 1 spray in your left nostril on your first day, followed by 1 spray in your right nostril on the second day.
  - Continue to switch nostrils for your dose each day.
- Your healthcare provider should check your nose before you start using Calcitonin Salmon (synthetic origin) Nasal Spray and often while you are using it.
- Tell your healthcare provider if you start to have discomfort (irritation) in your nose that bothers you while you use Calcitonin Salmon (synthetic origin) Nasal Spray.
- Your health care provider should prescribe calcium and vitamin D to help prevent low calcium levels in your blood while you use Calcitonin Salmon (synthetic origin) Nasal Spray.
- Take your calcium and vitamin D as your healthcare provider tells you to.
- There are 14 doses (2 mL fill) or 30 doses (3.7 mL fill) (sprays) of Calcitonin Salmon (synthetic origin) Nasal Spray in each bottle. After either 14 doses (2 mL fill) or 30 doses (3.7 mL fill), each spray may not give you the right amount of medicine, even if the bottle is not completely empty. Keep track of the number of doses of medicine used from your bottle.
- If you use too much Calcitonin Salmon (synthetic origin) Nasal Spray, call your healthcare provider or go to the nearest hospital emergency room right away.

What are the possible side effects of Calcitonin Salmon (synthetic origin) Nasal Spray?

Calcitonin Salmon (synthetic origin) Nasal Spray may cause serious side effects, including:

- allergic reactions
  Some people have had an allergic reaction when using calcitonin salmon nasal spray. Some reactions may be serious and can be life threatening. Call your healthcare provider or go to the nearest hospital emergency room right away if you have any of these symptoms of an allergic reaction.
  - trouble breathing
  - swelling of your face, throat or tongue
  - fast heartbeat
  - chest pain
  - feel dizzy or faint
  If you might be allergic to calcitonin salmon, your healthcare provider should do a skin test before you use Calcitonin Salmon (synthetic origin) Nasal Spray.
- low calcium levels in your blood (hypocalcemia)
  Calcitonin Salmon (synthetic origin) Nasal Spray may lower the calcium levels in your blood. If you have low blood calcium before you start using Calcitonin Salmon (synthetic origin) Nasal Spray, it may get worse during treatment. Your low blood calcium must be treated before you use Calcitonin Salmon (synthetic origin) Nasal Spray. Most people with low blood calcium levels do not have symptoms, but some people may have symptoms. Call your healthcare provider right away if you have any of these symptoms of low blood calcium:
  - numbness or tingling in your fingers, toes, or around your mouth
  Your healthcare provider should:
  - do blood tests while you use Calcitonin Salmon (synthetic origin) Nasal Spray
  - prescribe calcium and vitamin D to help prevent low calcium levels in your blood while you use Calcitonin Salmon (synthetic origin) Nasal Spray.
  Take your calcium and vitamin D as your healthcare provider tells you to.
- nose irritation
  Irritation of your nose can happen while you are using Calcitonin Salmon (synthetic origin) Nasal Spray, especially if you are over 65 years of age. Call your healthcare provider right way if you have any of these symptoms of nose irritation:
  - crusting
  - dryness
  - redness or swelling
  - nose sores (ulcers)
  - nose bleeds
  Your healthcare provider may stop your treatment with Calcitonin Salmon (synthetic origin) Nasal Spray until your nose irritation symptoms go away.
- risk of cancer
  People who use calcitonin salmon, the medicine in Calcitonin Salmon (synthetic origin) Nasal Spray, may have an increased risk of cancer.
- increase of certain cells (sediment) in your urine
  Your healthcare provider should test your urine often while you are using Calcitonin Salmon (synthetic origin) Nasal Spray.

The most common side effects of Calcitonin Salmon (synthetic origin) Nasal Spray include:

- back pain
- muscle aches
- headache
- runny nose

These are not all the possible side effects of Calcitonin Salmon (synthetic origin) Nasal Spray. For more information, ask your healthcare provider or pharmacist.

Tell your healthcare provider right away if you have any side effect that bothers you or does not go away.

Call your doctor for medical advice about side effects. You may report side effects to FDA at 1-800-FDA-1088.

How do I store Calcitonin Salmon (synthetic origin) Nasal Spray?

- Store open bottles of Calcitonin Salmon (synthetic origin) Nasal Spray at room temperature between 20°C to 25°C (68°F to 77°F) for 30 days (2 mL fill) or 35 days (3.7 mL fill).
- Store unopened bottles of Calcitonin Salmon (synthetic origin) Nasal Spray in the refrigerator between 2°C to 8°C (36°F to 46°F). Do not freeze.
- Store Calcitonin Salmon (synthetic origin) Nasal Spray bottles in an upright position.
- Safely throw away Calcitonin Salmon (synthetic origin) Nasal Spray in the trash after you have used 14 doses (2 mL fill) or 30 doses (3.7 mL fill) (sprays).

Keep Calcitonin Salmon (synthetic origin) Nasal Spray and all other medicines out of the reach of children.

General information about the safe and effective use of Calcitonin Salmon (synthetic origin) Nasal Spray.

Medicines are sometimes prescribed for purposes other than those listed in a Patient Information leaflet. Do not use Calcitonin Salmon (synthetic origin) Nasal Spray for a condition for which it was not prescribed. Do not give Calcitonin Salmon (synthetic origin) Nasal Spray to other people, even if they have the same symptoms you have. It may harm them.

This Patient Information summarizes the most important information about Calcitonin Salmon (synthetic origin) Nasal Spray. If you would like more information, talk with your healthcare provider. You can ask your pharmacist or healthcare provider for information about Calcitonin Salmon (synthetic origin) Nasal Spray that is written for health professionals.

For more information, call 1-800-706-5575.

What are the ingredients in Calcitonin Salmon (synthetic origin) Nasal Spray?

Active Ingredients: calcitonin salmon

Inactive Ingredients: benzalkonium chloride, hydrochloric acid, purified water and sodium chloride.

PRINCIPAL DISPLAY PANEL - PACKAGE CARTON LABEL

APOTEX CORP. NDC 60505-0823-6

Calcitonin Salmon (synthetic origin) Nasal Spray

(Calcitonin Salmon Nasal Solution, USP)

Rx

30 Doses per bottle

2200 USP Calcitonin Salmon Units/mL (200 USP Calcitonin Salmon Units/spray)

FOR INTRANASAL USE ONLY

REFRIGERATE UNTIL OPENED